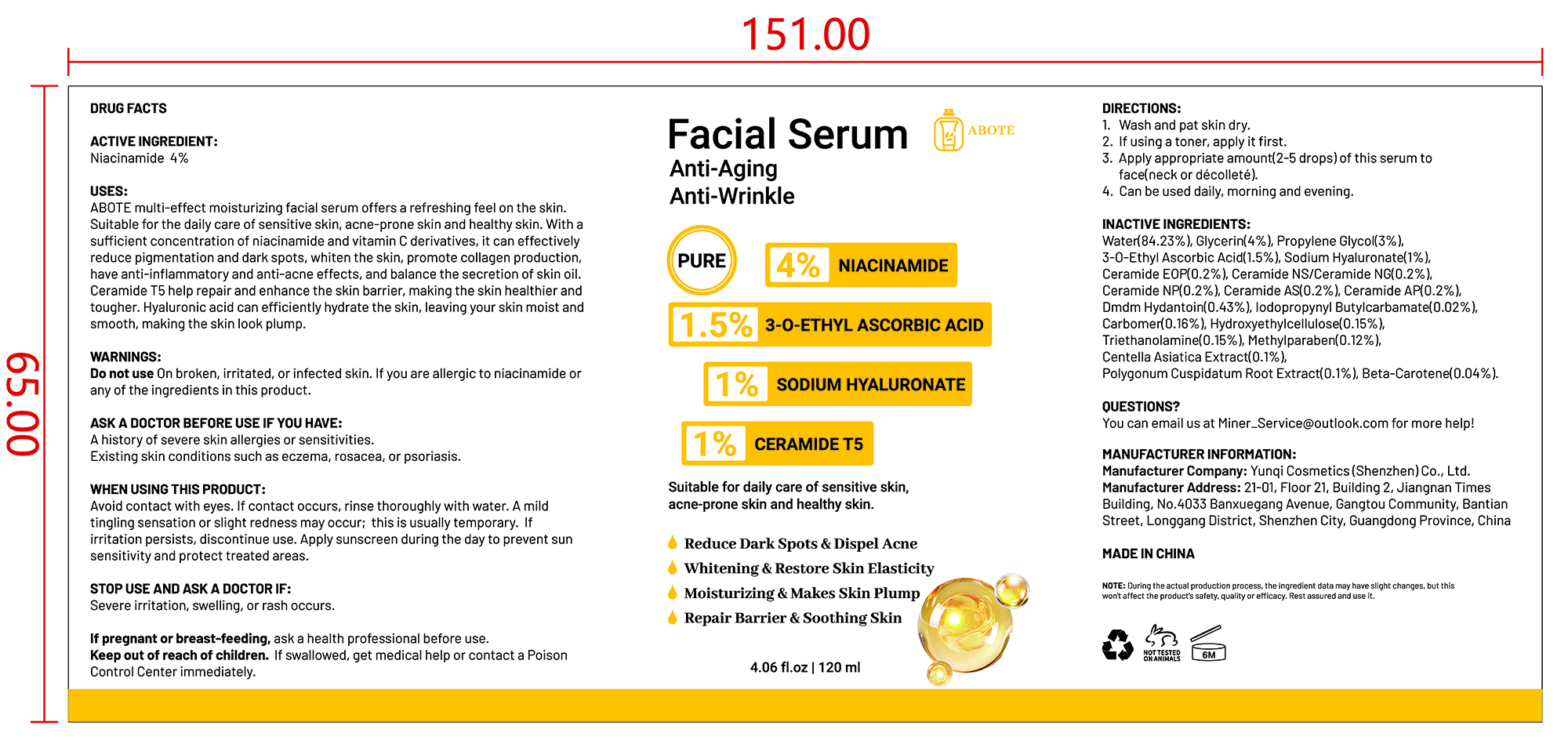 DRUG LABEL: Facial Serum
NDC: 84763-002 | Form: LIQUID
Manufacturer: Yunqi Cosmetics (Shenzhen) Co., Ltd
Category: otc | Type: HUMAN OTC DRUG LABEL
Date: 20241213

ACTIVE INGREDIENTS: NIACINAMIDE 4 g/100 mL
INACTIVE INGREDIENTS: CERAMIDE NG; IODOPROPYNYL BUTYLCARBAMATE; METHYLPARABEN; GLYCERIN; CERAMIDE 5; 3-O-ETHYL ASCORBIC ACID; CERAMIDE 9; CERAMIDE AP; CENTELLA ASIATICA TRITERPENOIDS; BETA-CAROTENE; CERAMIDE NP; CARBOMER; HYDROXYETHYLCELLULOSE; POLYGONUM CUSPIDATUM ROOT; PROPYLENE GLYCOL; SODIUM HYALURONATE; DMDM HYDANTOIN; TRIETHANOLAMINE; WATER

Facial Serum

Facial Serum

ACTIVE INGREDIENT

Niacinamide 4%

PURPOSE

Suitable for daily care of sensitive skin,acne-prone skin and healthy skin.

INDICATIONS AND USAGE

ABOTE multi-effect moisturizing facial serum offers a refreshing feel on the skin.Suitable for the daily care of sensitive skin, acne-prone skin and healthy skin. With asufficient concentration of niacinamide and vitamin C derivatives, it can effectivelyreduce pigmentation and dark spots, whiten the skin, promote collagen productionhave anti-inflammatory and anti-acne effects, and balance the secretion of skin oil.Ceramide T5 help repair and enhance the skin barrier, making the skin healthier andtougher. Hyaluronic acid can efficiently hydrate the skin, leaving your skin moist andsmooth, making the skin look plump.

Do not use On broken, irritated, or infected skin. lf you are allergic to niacinamide or any of the ingredients in this product.

ASK A DOCTOR BEFORE USE IF YOU HAVE:A history of severe skin allergies or sensitivities.Existing skin conditions such as eczema, rosacea, or psoriasis.

WHEN USING THIS PRODUCT:
Avoid contact with eyes. lf contact occurs, rinse thoroughly with water. A mildtingling sensation or slight redness may occur; this is usually temporary. lfirritation persists, discontinue use. Apply sunscreen during the day to prevent sunsensitivity and protect treated areas.

STOP USE AND ASK A DOCTOR IF:Severe irritation, swelling, or rash occurs.

KEEP OUT OF REACH OF CHILDREN

If pregnant or breast-feeding, ask a health professional before use.Keep out of reach of children. lf swallowed, get medical help or contact a PoisonControl Centerimmediately.

DOSAGE AND ADMINISTRATION

1. Wash and pat skin dry.

2. lf using a toner, apply it first.

3.Apply appropriate amount(2-5 drops) of this serum toface(neck or décolleté).
4. Can be used daily, morning and evening.

INACTIVE INGREDIENT

Water
Glycerin
Propylene Glycol
3-O-Ethyl Ascorbic Acid
Sodium Hyaluronate
Ceramide EOP
Ceramide NS/Ceramide NG
Ceramide NP
Ceramide AS
Ceramide AP
Dmdm Hydantoin
Iodopropynyl Butylcarbamate
Carbomer
Hydroxyethylcellulose
Triethanolamine
Methylparaben
Centella Asiatica Extract
Polygonum Cuspidatum Root Extract
Beta-Carotene